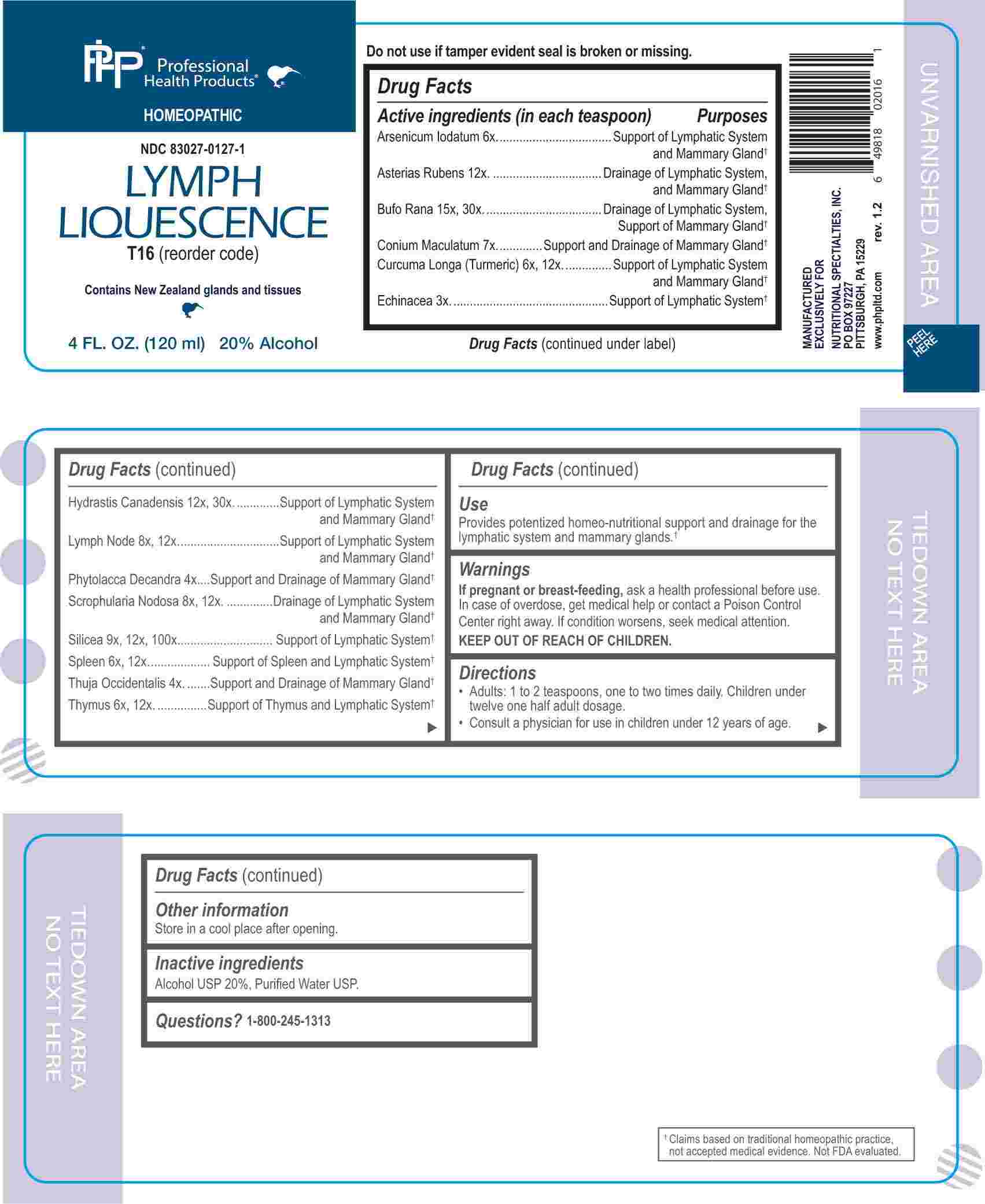 DRUG LABEL: Lymph Liquescence
NDC: 83027-0127 | Form: LIQUID
Manufacturer: Nutritional Specialties, Inc.
Category: homeopathic | Type: HUMAN OTC DRUG LABEL
Date: 20240905

ACTIVE INGREDIENTS: ECHINACEA ANGUSTIFOLIA WHOLE 3 [hp_X]/1 mL; PHYTOLACCA AMERICANA ROOT 4 [hp_X]/1 mL; THUJA OCCIDENTALIS LEAFY TWIG 4 [hp_X]/1 mL; ARSENIC TRIIODIDE 6 [hp_X]/1 mL; TURMERIC 6 [hp_X]/1 mL; BOS TAURUS SPLEEN 6 [hp_X]/1 mL; LAMB 6 [hp_X]/1 mL; CONIUM MACULATUM FLOWERING TOP 7 [hp_X]/1 mL; SUS SCROFA LYMPH 8 [hp_X]/1 mL; SCROPHULARIA NODOSA WHOLE 8 [hp_X]/1 mL; SILICON DIOXIDE 9 [hp_X]/1 mL; ASTERIAS RUBENS 12 [hp_X]/1 mL; GOLDENSEAL 12 [hp_X]/1 mL; BUFO BUFO CUTANEOUS GLAND 15 [hp_X]/1 mL
INACTIVE INGREDIENTS: WATER; ALCOHOL

DRUG FACTS:

ACTIVE INGREDIENTS:

(in each teaspoon) Arsenicum Iodatum 6X, Asterias Rubens 12X, Bufo Rana 15X, 30X, Conium Maculatum 7X, Curcuma Longa (Turmeric) 6X, 12X, Echinacea 3X, Hydrastis Canadensis 12X, 30X, Lymph Node 8X, 12X, Phytolacca Decandra 4X, Scrophularia Nodosa 8X, 12X, Silicea 9X, 12X, 100X, Spleen 6X, 12X, Thuja Occidentalis 4X, Thymus 6X, 12X.

PURPOSE:

Arsenicum Iodatum – Support of Lymphatic System and Mammary Gland,† Asterias Rubens – Drainage of Lymphatic System and Mammary Gland,† Bufo Rana – Drainage of Lymphatic System, Support of Mammary Gland, Conium Maculatum - Support and Drainage of Mammary Gland,† Curcuma Longa (Turmeric) – Support of Lymphatic System and Mammary Gland,† Echinacea – Support of Lymphatic System, Hydrastis Canadensis – Support of Lymphatic System and Mammary Gland,† Lymph Node - Support of Lymphatic System and Mammary Gland,† Phytolacca Decandra - Support and Drainage of Mammary Gland,† Scrophularia Nodosa - Drainage of Lymphatic System and Mammary Gland,† Silicea - Support of Lymphatic System,† Spleen – Support of Spleen and Lymphatic System,† Thuja Occidentalis - Support and Drainage of Mammary Gland,† Thymus – Support of Thymus and Lymphatic System†

USES:

Provides potentized homeo-nutritional support and drainage for the lymphatic system and mammary glands.†

†Claims based on traditional homeopathic practice, not accepted medical evidence. Not FDA evaluated.

WARNINGS:

If pregnant or breast-feeding, ask a health professional before use.

In case of overdose, get medical help or contact a Poison Control Center right away.

If condition worsens, seek medical attention.

KEEP OUT OF REACH OF CHILDREN

Do not use if tamper evident seal is broken or missing.

Store in a cool place after opening

KEEP OUT OF REACH OF CHILDREN:

In case of overdose, get medical help or contact a Poison Control Center right away.

DIRECTIONS:

• Adults: 1 to 2 teaspoons, one to two times daily. Children under twelve one half adult dosage.

• Consult a physician for use in children under 12 years of age.

INACTIVE INGREDIENTS:

Alcohol USP 20%, Purified Water USP.

QUESTIONS:

MANUFACTURED EXCLUSIVELY FOR

NUTRITIONAL SPECIALTIES, INC.

PO BOX 97227

PITTSBURG, PA 15229

www.phpltd.com

PACKAGE LABEL DISPLAY:

Professional

Health Products

HOMEOPATHIC

NDC 83027-0127-1

LYMPH

LIQUESCENCE

4 FL. OZ (120 ml)